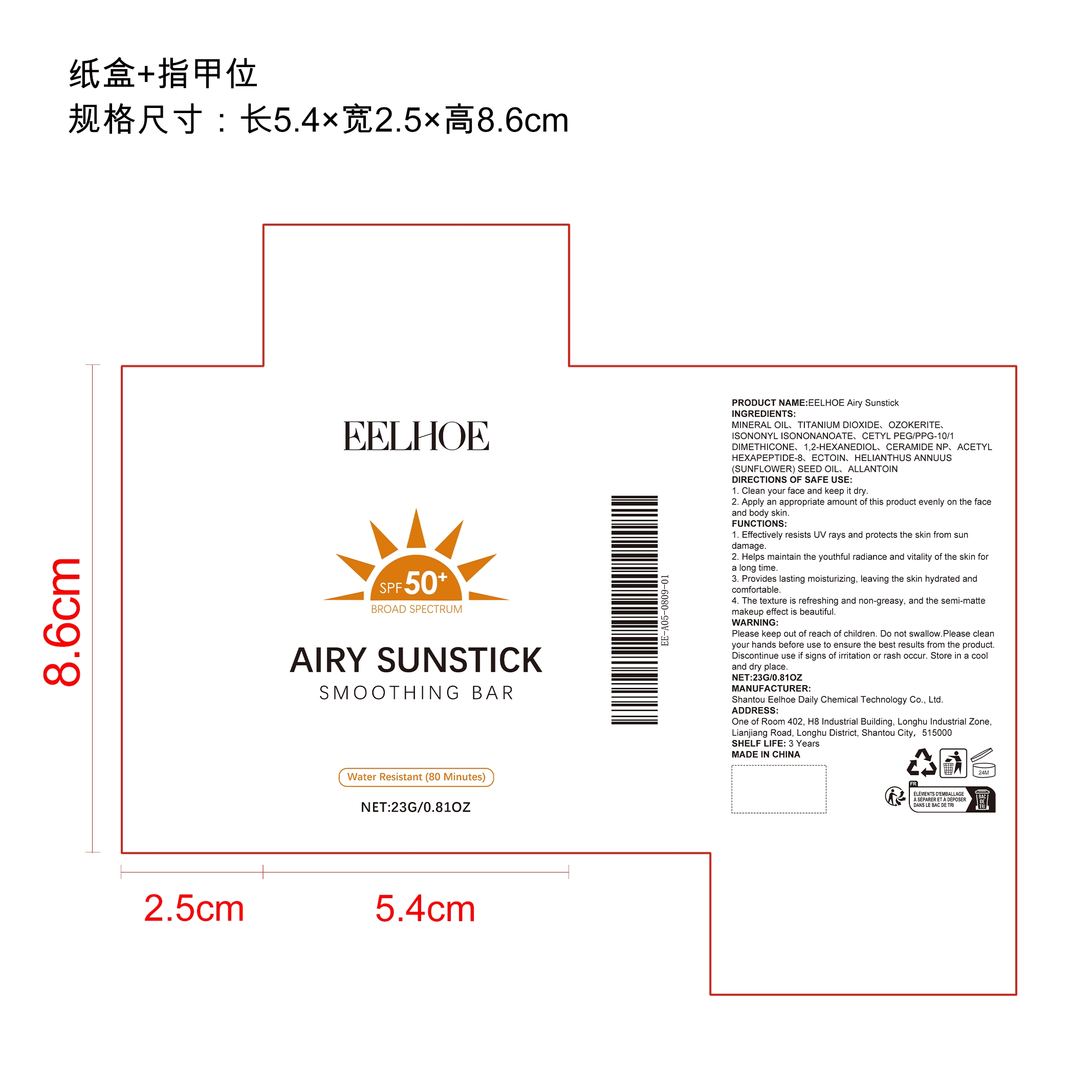 DRUG LABEL: EELHOE Airy Sunstick
NDC: 85064-023 | Form: CREAM
Manufacturer: Shantou Eelhoe Daily Chemical Technology Co., Ltd.
Category: otc | Type: HUMAN OTC DRUG LABEL
Date: 20251205

ACTIVE INGREDIENTS: HELIANTHUS ANNUUS (SUNFLOWER) SEED OIL 0.0046 mg/23 mg
INACTIVE INGREDIENTS: MINERAL OIL 9.407 mg/23 mg; TITANIUM DIOXIDE 5.75 mg/23 mg; CERESIN 4.6 mg/23 mg; CETYL PEG/PPG-10/1 DIMETHICONE (HLB 2) 0.805 mg/23 mg; ALLANTOIN 0.0046 mg/23 mg; ISONONYL ISONONANOATE 2.3 mg/23 mg; CERAMIDE NP 0.0046 mg/23 mg; ECTOIN 0.0046 mg/23 mg; 1,2-HEXANEDIOL 0.115 mg/23 mg; ACETYL HEXAPEPTIDE-8 0.0046 mg/23 mg

ACTIVE INGREDIENT

MINERAL OIL、TITANIUM DIOXIDE、OZOKERITE、ISONONYL ISONONANOATE、CETYL PEG/PPG-10/1 DIMETHICONE、1,2-HEXANEDIOL、CERAMIDE NP、ACETYL HEXAPEPTIDE-8、ECTOIN、ALLANTOIN

PURPOSE

1. Effectively resists UV rays and protects the skin from sun damage.

2. Helps maintain the youthful radiance and vitality of the skin for a long time.

3. Provides lasting moisturizing, leaving the skin hydrated and comfortable.

4. The texture is refreshing and non-greasy, and the semi-matte makeup effect is beautiful.

WHEN USING

1. Clean your face and keep it dry.

2. Apply an appropriate amount of this product evenly on the face and body skin.

WARNINGS

Please keep out of reach of children. Do not swallow.Please clean your hands before use to ensure the best results from the product. Discontinue use if signs of irritation or rash occur. Store in a cool and dry place.

DO NOT USE

Discontinue use if signs of irritation or rash occur.

STOP USE

Discontinue use if signs of irritation or rash occur.

KEEP OUT OF REACH OF CHILDREN

Please keep out of reach of children. Do not swallow.

KEEP OUT OF REACH OF CHILDREN

Please keep out of reach of children. Do not swallow.

STORAGE AND HANDLING

Store in a cool and dry place.

INACTIVE INGREDIENT

MINERAL OIL、TITANIUM DIOXIDE、OZOKERITE、ISONONYL ISONONANOATE、CETYL PEG/PPG-10/1 DIMETHICONE、1,2-HEXANEDIOL、CERAMIDE NP、ACETYL HEXAPEPTIDE-8、ECTOIN、ALLANTOIN

INDICATIONS AND USAGE

1. Clean your face and keep it dry.

2. Apply an appropriate amount of this product evenly on the face and body skin.

DOSAGE AND ADMINISTRATION

1. Clean your face and keep it dry.

2. Apply an appropriate amount of this product evenly on the face and body skin.